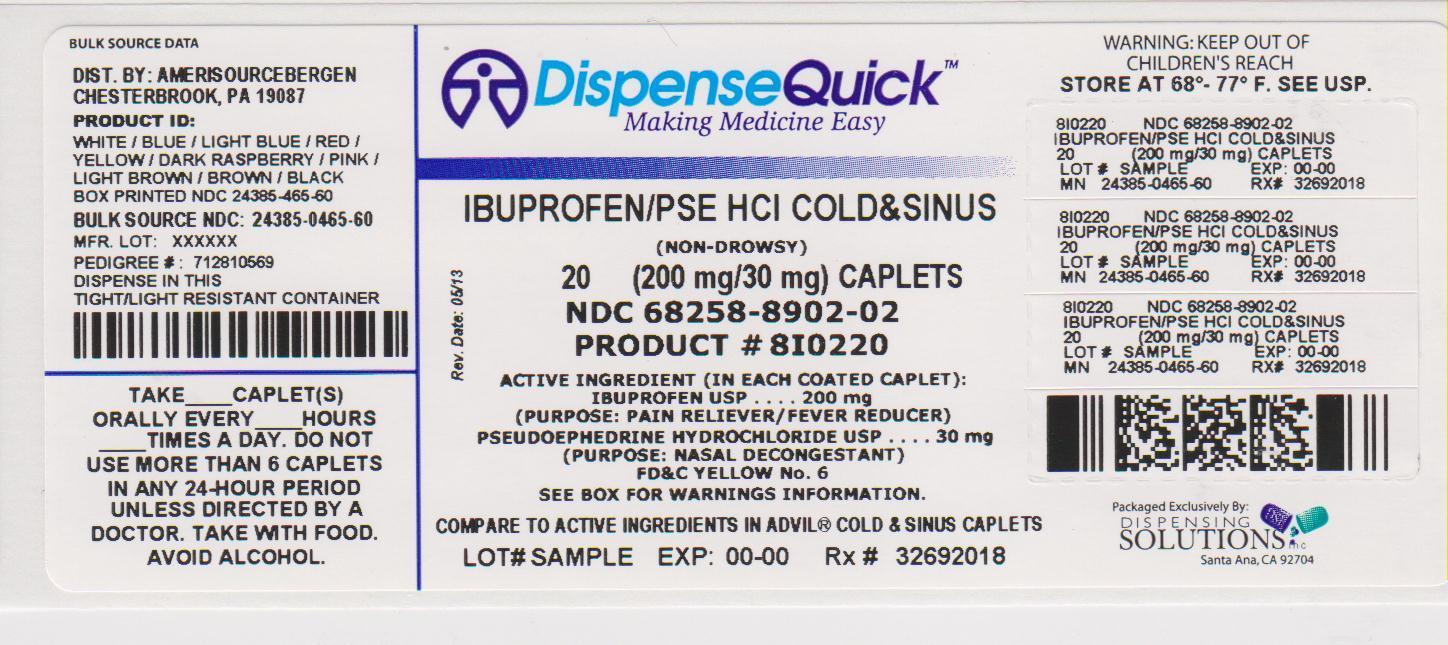 DRUG LABEL: Good Neighbor Pharmacy Ibuprofen Cold and Sinus
NDC: 68258-8902 | Form: TABLET
Manufacturer: Dispensing Solutions, Inc.
Category: otc | Type: HUMAN OTC DRUG LABEL
Date: 20130605

ACTIVE INGREDIENTS: IBUPROFEN 200 mg/1 1; PSEUDOEPHEDRINE HYDROCHLORIDE 30 mg/1 1
INACTIVE INGREDIENTS: ACACIA; CALCIUM CARBONATE; CARNAUBA WAX; SUCROSE; STARCH, CORN; CROSCARMELLOSE SODIUM; CROSPOVIDONE; FD&C BLUE NO. 2; FD&C RED NO. 40; FD&C YELLOW NO. 6; GELATIN; GUAR GUM; HYDROXYPROPYL CELLULOSE; KAOLIN; POWDERED CELLULOSE; POVIDONE; SILICON DIOXIDE; SODIUM BENZOATE; TALC; TITANIUM DIOXIDE; WHITE WAX; POLYETHYLENE GLYCOLS

Amerisource Bergen Ibuprofen Cold and Sinus Drug Facts

Active ingredient (in each caplet)

Ibuprofen, USP 200 mg (NSAID)*

Pseudoephedrine HCl, USP 30 mg

*nonsteroidal anti-inflammatory drug

Purpose

Pain reliever/Fever reducer

Nasal decongestant

Uses

temporarily relieves these symptoms associated with the common cold or flu:

- headache
- fever
- sinus pressure
- nasal congestion
- minor body aches and pains

Warnings

Allergy alert: Ibuprofen may cause a severe allergic reaction, especially in people allergic to aspirin. Symptoms may include:

- hives
- facial swelling
- asthma (wheezing)
- shock
- skin reddening
- rash
- blisters

If an allergic reaction occurs, stop use and seek medical help right away.

Stomach bleeding warning: This product contains an NSAID, which may cause severe stomach bleeding. The chance is higher if you:

- are age 60 or older
- have had stomach ulcers or bleeding problems
- take a blood thinning (anticoagulant) or steroid drug
- take other drugs containing prescription or nonprescription NSAIDs, [aspirin, ibuprofen, naproxen, or others]
- have 3 or more alcoholic drinks every day while using this product
- take more or for a longer time than directed

Do not use

- if you have ever had an allergic reaction to any other pain reliever/fever reducer
- if you are now taking a prescription monoamine oxidase inhibitor (MAOI) (certain drugs for depression, psychiatric, or emotional conditions, or Parkinson’s disease), or for 2 weeks after stopping the MAOI drug. If you do not know if your prescription drug contains an MAOI, ask a doctor or pharmacist before taking this product.
- in children under 12 years of age
- right before or after heart surgery

Ask a doctor before use if

- stomach bleeding warning applies to you
- you have problems or serious side effects from taking pain relievers or fever reducers
- you have a history of stomach problems, such as heartburn
- you have high blood pressure, heart disease, liver cirrhosis, kidney disease, asthma, thyroid disease, diabetes, or trouble urinating due to an enlarged prostate gland
- you are taking a diuretic

Ask a doctor or pharmacist before use if you are

- under a doctor’s care for any serious condition
- taking any other drug
- taking any other product that contains pseudoephedrine, or any other nasal decongestant
- taking aspirin for heart attack or stroke, because ibuprofen may decrease this benefit of aspirin

When using this product

- take with food or milk if stomach upset occurs
- the risk of heart attack or stroke may increase if you use more than directed or for longer than directed

Stop use and ask a doctor if

- you experience any of the following signs of stomach bleeding:
- feel faint
- vomit blood
- have bloody or black stools
- have stomach pain that does not get better
- symptoms continue or get worse
- any new symptoms appear
- you get nervous, dizzy, or sleepless
- fever gets worse or lasts more than 3 days
- nasal congestion lasts for more than 7 days
- redness or swelling is present in the painful area

If pregnant or breast-feeding,

ask a health professional before use. It is especially important not to use ibuprofen during the last 3 months of pregnancy unless definitely directed to do so by a doctor because it may cause problems in the unborn child or complications during delivery.

Keep out of reach of children.

In case of overdose, get medical help or contact a Poison Control Center right away. (1-800-222-1222)

Directions

- do not take more than directed
- the smallest effective dose should be used
- adults and children 12 years of age and over:
- take 1 caplet every 4 to 6 hours while symptoms persist. If symptoms do not respond to 1 caplet, 2 caplets may be used.
- do not use more than 6 caplets in any 24-hour period unless directed by a doctor
- children under 12 years of age: do not use

Other information

- store at 20-25°C (68-77°F). Avoid excessive heat above 40°C (104°F).
- read all warnings and directions before use. Keep carton.

Inactive ingredients

acacia, calcium carbonate, carnauba wax, confectioner’s sugar, corn starch, croscarmellose sodium, crospovidone, FD&C blue no. 2, FD&C red no. 40, FD&C yellow no. 6, gelatin, guar gum, hydrogenated vegetable oil, hydroxypropyl cellulose, kaolin, pharmaceutical ink, polyethylene glycol, powdered cellulose, povidone, pregelatinized starch, silicon dioxide, sodium benzoate, sucrose, talc, titanium dioxide, white wax

Questions or comments?

1-800-719-9260

Principal Display Panel

COMPARE TO ACTIVE INGREDIENTS IN ADVIL® COLD & SINUS

Non Drowsy

Ibuprofen Cold & Sinus

Ibuprofen 200 mg – Pain Reliever/Fever Reducer (NSAID)*

Pseudoephedrine HCl 30 mg – Nasal Decongestant

Tablets, USP

*nonsteroidal anti-inflammatory drug

Relieves Sinus Pressure, Nasal Congestion and Fever

See New Warnings Information

**OVAL-SHAPED TABLETS

NDC 68258-8902-02